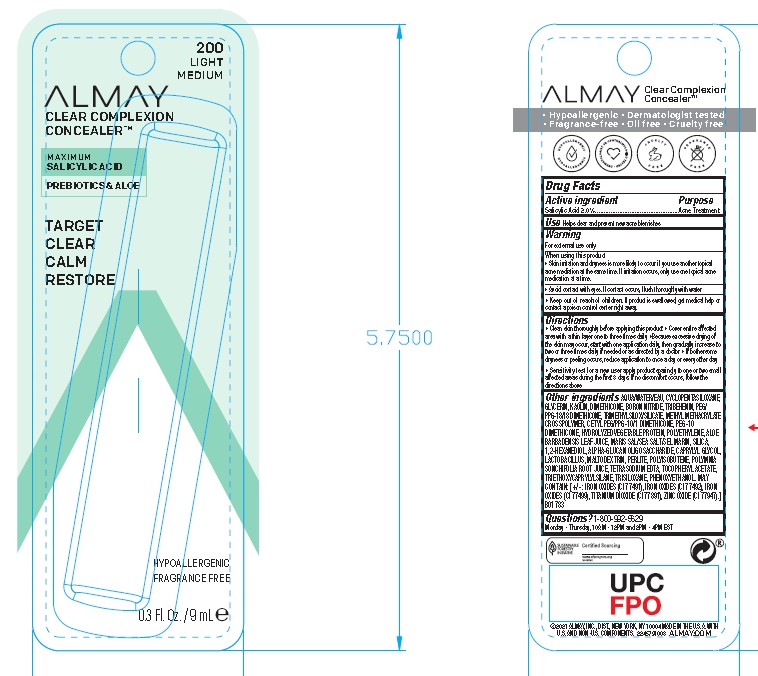 DRUG LABEL: ALMAY CLEAR COMPLEXION CONCEALER
NDC: 0311-0731 | Form: LIQUID
Manufacturer: ALMAY
Category: otc | Type: HUMAN OTC DRUG LABEL
Date: 20241231

ACTIVE INGREDIENTS: SALICYLIC ACID 2 mg/2 mL
INACTIVE INGREDIENTS: HYDROLYZED CORN PROTEIN (ENZYMATIC; 1500 MW); SODIUM BENZOATE; TETRASODIUM EDTA; SILICA; LACTOBACILLUS; MALTODEXTRIN; POTASSIUM SORBATE; PENTAERYTHRITYL TETRA-DI-T-BUTYL HYDROXYHYDROCINNAMATE; SMALLANTHUS SONCHIFOLIUS ROOT JUICE; CYCLOPENTASILOXANE; POLYETHYLENE; 1,2-HEXANEDIOL; .ALPHA.-GLUCAN OLIGOSACCHARIDE; WATER; CETYL PEG/PPG-10/1 DIMETHICONE (HLB 2); GLYCERIN; BORON NITRIDE; FERROSOFERRIC OXIDE; METHYL METHACRYLATE/GLYCOL DIMETHACRYLATE CROSSPOLYMER; PHENOXYETHANOL; POLYISOBUTYLENE (1000 MW); FERRIC OXIDE RED; FERRIC OXIDE YELLOW; SEA SALT; PEG-10 DIMETHICONE (600 CST); PERLITE; TRIBEHENIN; TRIETHOXYCAPRYLYLSILANE; TRIMETHYLSILOXYSILICATE (M/Q 0.66); ZINC OXIDE; PEG/PPG-18/18 DIMETHICONE; TRISILOXANE; CAPRYLYL GLYCOL; TITANIUM DIOXIDE; KAOLIN; ALPHA-TOCOPHEROL ACETATE; ALOE VERA LEAF; DIMETHICONE

ALMAY CLEAR COMPLEXION CONCEALER - FAIR

ACTIVE INGREDIENT

Active ingredient Purpose
Salicylic Acid 2.0%................................................Acne Treatment

OTHER INGREDIENTS

AQUA/WATER/EAU, CYCLOPENTASILOXANE, GLYCERIN, KAOLIN, DIMETHICONE, BORON NITRIDE, TRIBEHENIN, PEG/
PPG-18/18 DIMETHICONE, TRIMETHYLSILOXYSILICATE, METHYL METHACRYLATE CROSSPOLYMER, CETYL PEG/PPG-10/1 DIMETHICONE, PEG-10 DIMETHICONE, HYDROLYZED VEGETABLE PROTEIN, POLYETHYLENE, ALOE BARBADENSIS LEAF JUICE, MARIS SAL/SEA SALT/SEL MARIN, SILICA, 1,2-HEXANEDIOL, ALPHA-GLUCAN OLIGOSACCHARIDE, CAPRYLYL GLYCOL, LACTOBACILLUS, MALTODEXTRIN, PERLITE, POLYISOBUTENE, POLYMNIA SONCHIFOLIA ROOT JUICE, TETRASODIUM EDTA, TOCOPHERYL ACETATE, TRIETHOXYCAPRYLYLSILANE, TRISILOXANE, PHENOXYETHANOL. MAY
CONTAIN: [+/- : IRON OXIDES (CI 77491), IRON OXIDES (CI 77492), IRON OXIDES (CI 77499), TITANIUM DIOXIDE (CI 77891), ZINC OXIDE (CI 77947).]

USE

Helps clear and prevent new acne blemishes

WARNING

• Keep out of reach of children. If product is swallowed, get medical help or contact a poison control center right away.

DIRECTIONS

• Clean skin thoroughly before applying this product

• Cover entire affected area with a thin layer one to three times daily

• Because excessive drying of the skin may occur, start with one application daily, then gradually increase to two or three times daily if needed or as directed by a doctor

• If bothersome dryness or peeling occurs, reduce application to once a day or every other day
• Sensitivity test for a new user apply product sparingly to one or two small affected areas during the first 3 days. If no discomfort occurs, follow the directions above

WARNINGS

When using this product

• Skin irritation and dryness is more likely to occur if you use another topical acne mediation at the same time. If irritation occurs, only use one topical acne medication at a time.
• Avoid contact with eyes. If contact occurs, flush thoroughly with water

PURPOSE

Anti-Acne Treatment